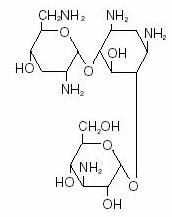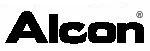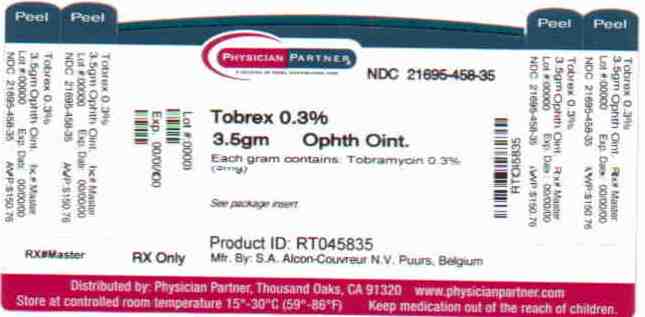 DRUG LABEL: Tobrex
NDC: 21695-458 | Form: OINTMENT
Manufacturer: Rebel Distributors Corp
Category: prescription | Type: HUMAN PRESCRIPTION DRUG LABEL
Date: 20101201

ACTIVE INGREDIENTS: tobramycin 3 mg/1 g
INACTIVE INGREDIENTS: chlorobutanol 5 mg/1 g; MINERAL OIL; PETROLATUM

Tobrex
tobramycin ophthalmic
ointment 0.3%

DESCRIPTION

TOBREX® (tobramycin ophthalmic ointment) 0.3% is a sterile topical ophthalmic antibiotic formulation prepared specifically for topical therapy of external ophthalmic infections.

Each gram of TOBREX (tobramycin ophthalmic ointment) 0.3% contains: Active: tobramycin 0.3% (3 mg). Preservative: chlorobutanol 0.5%. Inactives: mineral oil, white petrolatum.

Tobramycin is a water-soluble aminoglycoside antibiotic active against a wide variety of gram-negative and gram-positive ophthalmic pathogens.

The chemical structure of tobramycin is :

Molecular formula:

C18H37N5O9

Molecular weight:

467.52

Chemical name:

0-{3-amino-3-deoxy-α-D-gluco-pyranosyl-(1→4) }-0-{2,6-diamino-2,3,6-trideoxy-α-D-ribohexo-pyranosyl-(1→6) }-2-deoxystreptamine.

CLINICAL PHARMACOLOGY

In Vitro Data: In vitro studies have demonstrated tobramycin is active against susceptible strains of the following microorganisms: Staphylococci, including S. aureus and S. epidermidis (coagulase- positive and coagulase-negative), including penicillin-resistant strains.

Streptococci, including some of the Group A–beta-hemolytic species, some nonhemolytic species, and some Streptococcus pneumoniae.

Pseudomonas aeruginosa, Escherichia coli, Klebsiella pneumoniae, Enterobacter aerogenes, Proteus mirabilis, Morganella morganii, most Proteus vulgaris strains, Haemophilus influenzae and H. aegyptius, Moraxella lacunata, Acinetobacter calcoaceticus and some Neisseria species. Bacterial susceptibility studies demonstrate that in some cases, microorganisms resistant to gentamicin retain susceptibility to tobramycin.

INDICATIONS AND USAGE

TOBREX (tobramycin ophthalmic ointment) 0.3 % is a topical antibiotic indicated in the treatment of external infections of the eye and its adnexa caused by susceptible bacteria. Appropriate monitoring of bacterial response to topical antibiotic therapy should accompany the use of TOBREX (tobramycin ophthalmic ointment) 0.3%. Clinical studies have shown tobramycin to be safe and effective for use in children.

CONTRAINDICATIONS

TOBREX (tobramycin ophthalmic ointment) 0.3% is contraindicated in patients with known hypersensitivity to any of its components.

WARNINGS

NOT FOR INJECTION INTO THE EYE. Sensitivity to topically applied aminoglycosides may occur in some patients. If a sensitivity reaction to TOBREX (tobramycin ophthalmic ointment) 0.3 % occurs, discontinue use.

PRECAUTIONS

General

As with other antibiotic preparations, prolonged use may result in overgrowth of nonsusceptible organisms, including fungi. If superinfection occurs, appropriate therapy should be initiated. Ophthalmic ointments may retard corneal wound healing.

Cross-sensitivity to other aminoglycoside antibiotics may occur; if hypersensitivity develops with this product, discontinue use and institute appropriate therapy.

Patients should be advised not to wear contact lenses if they have signs and symptoms of ocular infections.

Information For Patients

Do not touch tube tip to any surface, as this may contaminate the ointment.

Do not use the product if the imprinted carton seals have been damaged, or removed.

Pregnancy Category B

Reproduction studies in three types of animals at doses up to thirty-three times the normal human systemic dose have revealed no evidence of impaired fertility or harm to the fetus due to tobramycin. There are, however, no adequate and well-controlled studies in pregnant women. Because animal studies are not always predictive of human response, this drug should be used during pregnancy only if clearly needed.

Nursing Mothers

Because of the potential for adverse reactions in nursing infants from TOBREX® (tobramycin ophthalmic ointment) 0.3 %, a decision should be made whether to discontinue nursing the infant or discontinue the drug, taking into account the importance of the drug to the mother.

Pediatric Use

Safety and effectiveness in pediatric patients below the age of 2 months has not been established.

Geriatric Use

No overall clinical differences in safety or effectiveness have been observed between the elderly and other adult patients.

ADVERSE REACTIONS

The most frequent adverse reactions to TOBREX (tobramycin ophthalmic ointment) 0.3% are hypersensitivity and localized ocular toxicity, including lid itching and swelling, and conjunctival erythema. These reactions occur in less than three of 100 patients treated with TOBREX (tobramycin ophthalmic ointment) 0.3%. Similar reactions may occur with the topical use of other aminoglycoside antibiotics. Other adverse reactions have not been reported from TOBREX (tobramycin ophthalmic ointment) 0.3% therapy; however, if topical ocular tobramycin is administered concomitantly with systemic aminoglycoside antibiotics, care should be taken to monitor the total serum concentration. In clinical trials, TOBREX (tobramycin ophthalmic ointment) 0.3% produced significantly fewer adverse reactions (3.7%) than did GARAMYCIN® Ophthalmic Ointment (10.6%).

OVERDOSAGE

Clinically apparent signs and symptoms of an overdose of TOBREX (tobramycin ophthalmic ointment) 0.3% (punctate keratitis, erythema, increased lacrimation, edema and lid itching) may be similar to adverse reaction effects seen in some patients.

DOSAGE AND ADMINISTRATION

In mild to moderate disease, apply a half-inch ribbon into the affected eye(s) two or three times per day. In severe infections, instill a half-inch ribbon into the affected eye(s) every three to four hours until improvement, following which treatment should be reduced prior to discontinuation.

How to Apply TOBREX (tobramycin ophthalmic ointment) 0.3%:

1. Tilt your head back.

2. Place a finger on your cheek just under your eye and gently pull down until a ‘‘V’’ pocket is formed between your eyeball and your lower lid.

3. Place a small amount (about 1/2 inch) of TOBREX (tobramycin ophthalmic ointment) 0.3 % in the ‘‘V’’ pocket. Do not let the tip of the tube touch your eye.

4. Look downward before closing your eye.

HOW SUPPLIED

3.5g STERILE ointment supplied in an aluminum tube with a white polyethylene tip and white polyethylene cap (NDC 0065-0644-35), containing tobramycin 0.3% (3 mg/g).

Storage: Store at 8° - 27°C (46°- 80°F).

Rx Only

Manufactured for:

ALCON LABORATORIES, INC.

Fort Worth, Texas 76134 USA

Manufactured by:

S.A. ALCON-COUVREUR N.V.

Puurs, Belgium

Repackaged by:

REBEL DISTRIBUTORS CORP

Thousand Oaks, CA 91320